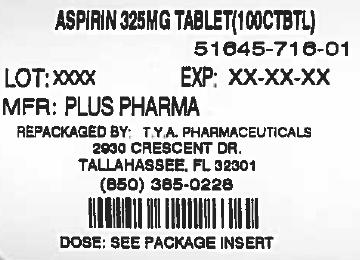 DRUG LABEL: Plus Pharma
                                    
NDC: 64725-0716 | Form: TABLET
Manufacturer: TYA Pharmaceuticals
Category: otc | Type: HUMAN OTC DRUG LABEL
Date: 20140929

ACTIVE INGREDIENTS: ASPIRIN 81 mg/1 1
INACTIVE INGREDIENTS: STARCH, CORN; POVIDONES

Drug Facts

Active ingredient (in each tablet)

Aspirin 325 mg (NSAID)*

* nonsteroidal anti-inflammatory drug

Purposes

Pain reliever/fever reducer

Uses

for temporary relief of

- headache
- muscular aches
- backache
- minor pain of arthritis
- the common cold
- toothache
- menstrual cramps
- minor aches and pains
- temporarily reduces fever

Warnings

Children and teenagers who have or are recovering from chicken pox or flu- like symptoms should not use this product. When using this product, if changes in behavior with nausea and vomiting occur, consult a doctor because these symptoms could be an early sign of Reye's syndrome, a rare but serious illness. Reye's syndrome:

Aspirin may cause a severe allergic reaction, which may include Allergy alert:

- hives
- facial swelling
- asthma(wheezing)
- shock

This product contains a nonsteroidal anti-inflammatory drug (NSAID), which may cause severe stomach bleeding. The chance is higher if you Stomach bleeding warning:

- are age 60 or older
- have had stomach ulcers or bleeding problems
- take a blood thinning (anticoagulant) or steroid drug
- take other drugs containing prescription or nonprescription NSAIDs (aspirin, ibuprofen, naproxen, or others)
- have 3 or more alcoholic drinks every day while using this product
- take more or for a longer time than directed

Do not use

with any other product containing Aspirin or if you have ever had an allergic reaction to aspirin or other pain relievers/fever reducers.

Ask a doctor before use if

- stomach bleeding warning applies to you
- you have a history of stomach problems, such as heartburn
- you have high blood pressure, heart disease, liver cirrhosis or kidney disease
- you are taking a diuretic

Ask a doctor or pharmacist before use if you are

taking a prescription drug for

- anticoagulation (blood thinning)
- gout
- diabetes
- arthritis

Stop use and ask a doctor if

- you experience any of the following signs of stomach bleeding
- feel faint
- vomit blood
- have bloody or black stools
- have stomach pain that does not get better
- pain gets worse or lasts more than 10 days
- fever gets worse or lasts more than 3 days
- new symptoms occur
- ringing in the ears or hearing loss occurs
- redness or swelling is present

PREGNANCY OR BREAST FEEDING

, ask a health professional before use. It is especially important not to use Aspirin during last 3 months of pregnancy unless definitely directed to do so by a doctor because it may cause problems in the unborn child or complications during delivery. If pregnant or breast-feeding

Keep out of reach of children.

In case of overdose, get medical help or contact a Poison Control Center right away.

Directions

- Drink a full glass of water with each dose
- Do not take more than directed
- take 1 to 2 tablets every 4 hours, or 3 tablets every 6 hours as needed. Do not take more than 12 tablets in 24 hours Adults and children 12 years and older:
- ask a doctor Children under 12:

Other information

- Do not use if imprinted safety seal under cap is broken or missing.
- Store at room temperature

Inactive ingredients

Corn Starch, Povidone.

Questions?

If you have any questions or comments, or to report an adverse event, please contact (800) 795-9775.